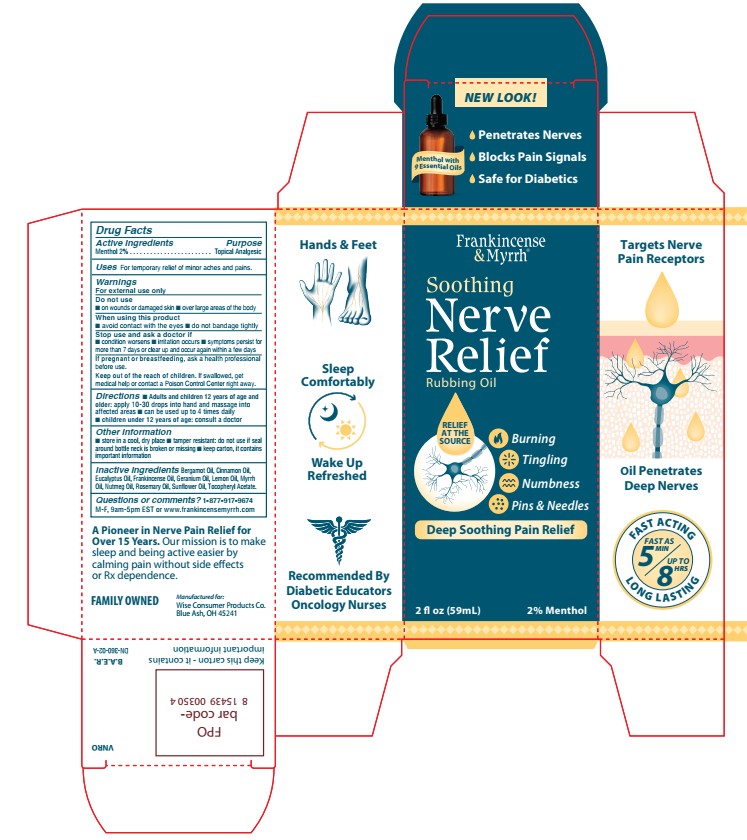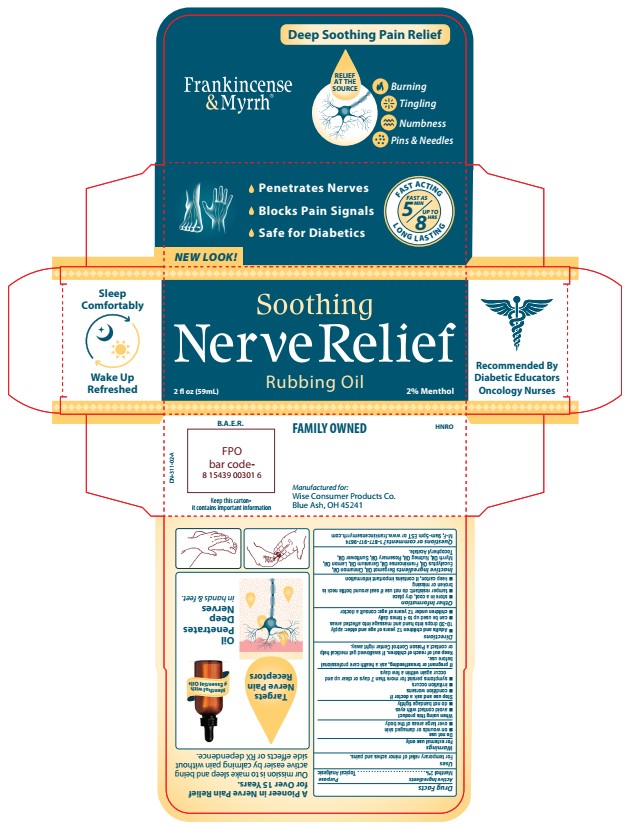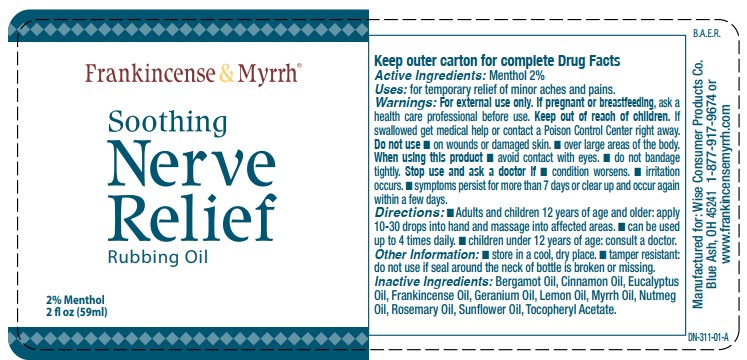 DRUG LABEL: Soothing Nerve Relief
NDC: 42346-360 | Form: OIL
Manufacturer: Wise Consumer Products
Category: otc | Type: HUMAN OTC DRUG LABEL
Date: 20251226

ACTIVE INGREDIENTS: MENTHOL 20 mg/1 mL
INACTIVE INGREDIENTS: MYRRH OIL; FRANKINCENSE OIL; .ALPHA.-TOCOPHEROL ACETATE; CINNAMON OIL; GERANIUM OIL, ALGERIAN TYPE; LEMON OIL; NUTMEG OIL; SUNFLOWER OIL; ROSEMARY OIL; BERGAMOT OIL; EUCALYPTUS OIL

Soothing Nerve Relief Rubbing Oil

Active ingredient

Menthol 2%

Purpose

Menthol 2%...............Topical Analgesic

Uses

For temporary relief of minor aches and pains.

Warnings

For external use only

Do not use

 on wounds or damaged skin  over large areas of the body

When using this product

 avoid contact with the eyes  do not bandage tightly

Stop use and ask a doctor if

 condition worsens  irritation occurs  symptoms persist formore than 7 days or clear up and occur again within a few days

PREGNANCY OR BREAST FEEDING

If pregnant or breastfeeding, ask a health professionalbefore use.

KEEP OUT OF REACH OF CHILDREN

Keep out of the reach of children. If swallowed, get medical help or contact a Poison Control Center right away.

Directions

 Adults and children 12 years of age andolder: apply 10-30 drops into hand and massage into affected areas  can be used up to 4 times daily  children under 12 years of age: consult a doctor

Other information

 store in a cool, dry place  tamper resistant: do not use if sealaround bottle neck is broken or missing  keep carton, it containsimportant information

Inactive ingredients

Bergamot Oil, Cinnamon Oil,Eucalyptus Oil, Frankincense Oil, Geranium Oil, Lemon Oil, Myrrh Oil, Nutmeg Oil, Rosemary Oil, Sunflower Oil, Tocopheryl Acetate

Questions or comments?

1-877-917-9674 M-F, 9am-5pm EST or www.frankincensemyrrh.com

PACKAGE LABEL

Frankincense & Myrrh

Soothing Nerve Relief Rubbing Oil

Relief at the Source

Burning

Tingling

Numbness

Pins & Needls

Deep Soothing Pain Relief

2 fl oz (59 mL)

2% Menthol